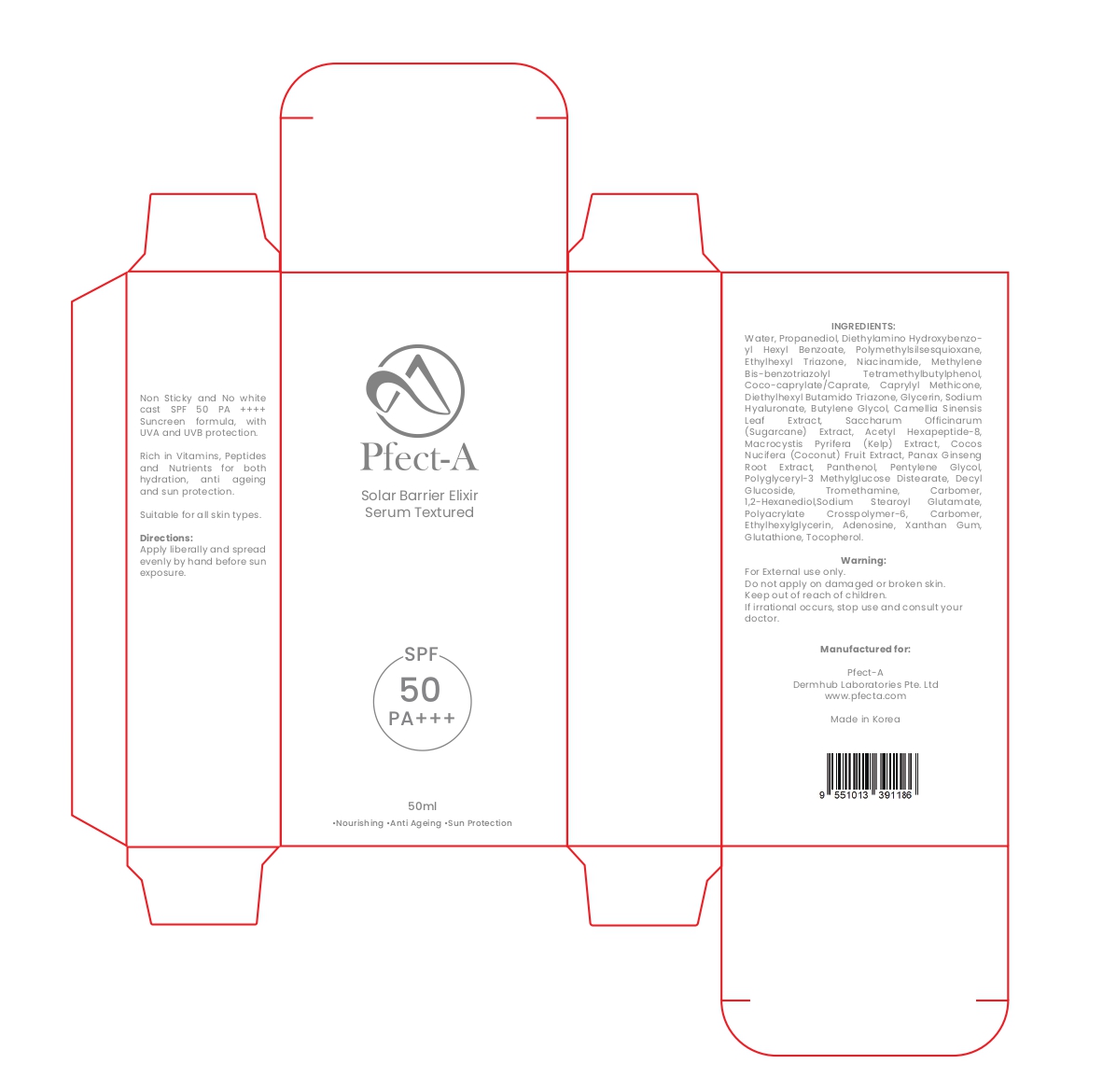 DRUG LABEL: Pfect A solar barrier Serum Textured
NDC: 84755-0002 | Form: ELIXIR
Manufacturer: KRX RESOURCES SDN. BHD.
Category: otc | Type: HUMAN OTC DRUG LABEL
Date: 20251018

ACTIVE INGREDIENTS: ETHYLHEXYL TRIAZONE 1.5 mg/50 mL; DIETHYLAMINO HYDROXYBENZOYL HEXYL BENZOATE 2.5 mg/50 mL
INACTIVE INGREDIENTS: CARBOMER 934; POLYGLYCERYL-3 METHYLGLUCOSE DISTEARATE; WATER; POLYMETHYLSILSESQUIOXANE (4.5 MICRONS); PEG-9 DIGLYCIDYL ETHER/SODIUM HYALURONATE CROSSPOLYMER; CARBOMER 980; GLUTATHIONE; TOCOPHEROL; ADENOSINE; GLYCERIN; XANTHAN GUM; ETHYLHEXYL CAPRYLATE/CAPRATE; NIACINAMIDE; PANTHENOL; DECYL GLUCOSIDE; TROMETHAMINE; SACCHARUM OFFICINARUM STEM FRUCTOOLIGOSACCHARIDES; ACETYL HEXAPEPTIDE-8; PENTYLENE GLYCOL; ETHYLHEXYLGLYCERIN; SODIUM STEAROYL GLUTAMATE; 1,2-HEXANEDIOL; PROPANEDIOL; BUTYLENE GLYCOL

DOSAGE AND ADMINISTRATION

Directions: Apply liberally and spread evenly by hand before sun exposure.

WARNINGS

Warning: For External use only. Do not apply on damaged or broken skin. Keep out of reach of children. If irrational occurs, stop use and consult your doctor.

Inactive Ingredients:
WATER, PROPANEDIOL, DIETHYLAMINO HYDROXYBENZOYL HEXYL BENZOATE, POLYMETHYLSILSESQUIOXANE, ETHYLHEXYL TRIAZONE, NIACINAMIDE, METHYLENE BIS- BENZOTRIAZOLYL TETRAMETHYLBUTYLPHENOL, COCO- CAPRYLATE/CAPRATE, CAPRYLYL METHICONE, DIETHYLHEXYL BUTAMIDO TRIAZONE, GLYCERIN, SODIUM HYALURONATE, BUTYLENE GLYCOL, CAMELLIA SINENSIS LEAF EXTRACT, SACCHARUM OFFICINARUM (SUGARCANE) EXTRACT, ACETYL HEXAPEPTIDE-8, MACROCYSTIS PYRIFERA (KELP) EXTRACT, COCOS NUCIFERA (COCONUT) FRUIT EXTRACT, PANAX GINSENG ROOT EXTRACT, PANTHENOL, PENTYLENE GLYCOL, POLYGLYCERYL-3 METHYLGLUCOSE DISTEARATE, DECYL GLUCOSIDE, TROMETHAMINE, CARBOMER, 1,2- HEXANEDIOL,SODIUM STEAROYL GLUTAMATE, POLYACRYLATE CROSSPOLYMER-6, CARBOMER, ETHYLHEXYLGLYCERIN, ADENOSINE, XANTHAN GUM, GLUTATHIONE, TOCOPHEROL.

INDICATIONS AND USAGE

Non Sticky and No white cast SPF 50 PA ++++ Suncreen formula, with UVA and UVB protection. Rich in Vitamins, Peptides and Nutrients for both hydration, anti ageing and sun protection. Suitable for all skin types.

Keep out of reach of children

PURPOSE

•Nourishing •Anti Ageing •Sun Protection

Non Sticky and No white cast SPF 50 PA ++++ Suncreen formula, with UVA and UVB protection. Rich in Vitamins, Peptides and Nutrients for both hydration, anti ageing and sun protection. Suitable for all skin types. Directions: Apply liberally and spread evenly by hand before sun exposure.

Active:
HYDROXYBENZOYL HEXYL BENZOATE 5%
ETHYLHEXYL TRIAZONE 3%

PACKAGE LABEL

Pfect-A solar barrier Elixir Serum Textured